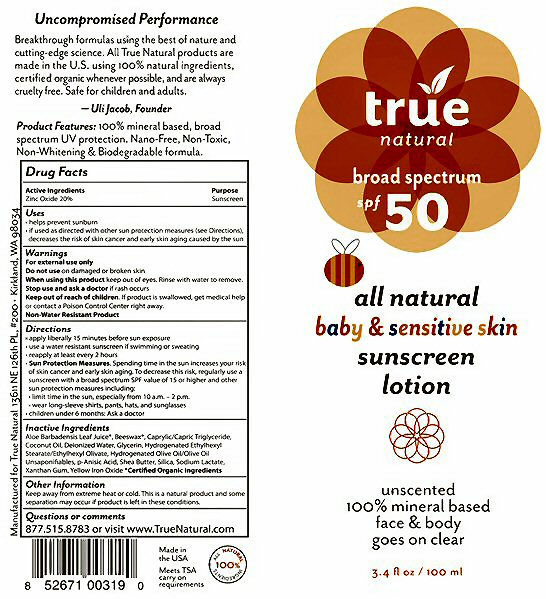 DRUG LABEL: True Natural broad spectrum spf 50
NDC: 76245-219 | Form: LOTION
Manufacturer: True Nature Group, Inc.
Category: otc | Type: HUMAN OTC DRUG LABEL
Date: 20120320

ACTIVE INGREDIENTS: ZINC OXIDE 20 mL/100 mL
INACTIVE INGREDIENTS: ALOE VERA LEAF; YELLOW WAX; MEDIUM-CHAIN TRIGLYCERIDES; COCONUT OIL; WATER; GLYCERIN; ETHYLHEXYL OLEATE; OLIVE OIL; P-ANISIC ACID; SHEA BUTTER; SILICON DIOXIDE; SODIUM LACTATE; XANTHAN GUM; FERRIC OXIDE YELLOW

Active Ingredients Section

Drug Facts:
Active Ingredients
Zinc Oxide 20%

Purpose Section

Purpose

Sunscreen

Keep Out Of Reach Of Children Section

Keep out of reach of children. If product swallowed, get medical help or contact a Poison Control Center right away.

Uses Section

Uses
* Helps prevent sunburn
* If used as directed with other sun protection measures (see Directions), decreases the risk of skin cancer and early skin aging caused by the sun

Warnings Section

Warnings
For external use only
Do not use on damaged or broken skin
When using this product keep out of eyes. Rinse with water to remove.
Stop use and ask a doctor if rash occurs
If product is swallowed, get medical help or contact a Poison Control Center right away.
Non-Water Resistant Product

Directions Section

Directions
* apply liberally 15 minutes before sun exposure
* use a water resistant sunscreen if swimming or sweating
* reapply at least every 2 hours
* Sun Protection Measures. Spending time in the sun increases your risk of skin cancer and early skin aging. To decrease this risk, regularly use a sunscreen with a broad spectrum SPF value of 15 or higher and other sun protection measures including:
* limit time in the sun, especially from 10 a.m. - 2 p.m.
* wear long-sleeve shirts, pants, hat, and sunglasses
* children under 6 months; Ask a doctor

Inactive Ingredients Section

Inactive Ingredients
Aloe Barbadensis Leaf Juice, Beeswax, Caprylic/Capric Triglyceride, Coconut Oil, Deionized Water, Fragrance (natural), Glycerin, Hydrogenated Ethylhexyl Stearate/Ethylhexyl Olivate, Hydrogenated Olive/Olive Oil Unsaponifiables, p-Anisic Acid, Shea Butter, Silica, Sodium Lactate, Xanthan Gum, Yellow Iron Oxide
Certified Organic Ingredients

Other Information Section

Other Information
Keep away from extreme heat or cold. This is a natural product and some separation may occur if product is left in these conditions.

Questions or Comments Section

Questions or comments
877.515.8783 or visit www.TrueNatural.com

Package Label

true natural broad spectrum spf 50 all natural baby and sensitive skin sunscreen lotion unscented 100% mineral based face and body goes on clear
3.4 fl oz / 100 ml
Uncompromised Performance
Breakthrough formulas using the best of nature and cutting-edge science. All True Natural products are made in the U.S. using 100% natural ingredients, certified organic whenever possible, and are always cruelty free. Safe for children and adults. Uli Jacob, Founder
Product Features: 100% mineral based, broad spectrum UV protection. Nano-Free, Non-Toxic, Non-Whitening and Biodegradable formula.
Manufactured for True Natural 13611 NE 126th PL, #200. Kirkland, WA 98034
Made in the USA Meets TSA carry-on requirements ALL NATURAL 100% INGREDIENTS